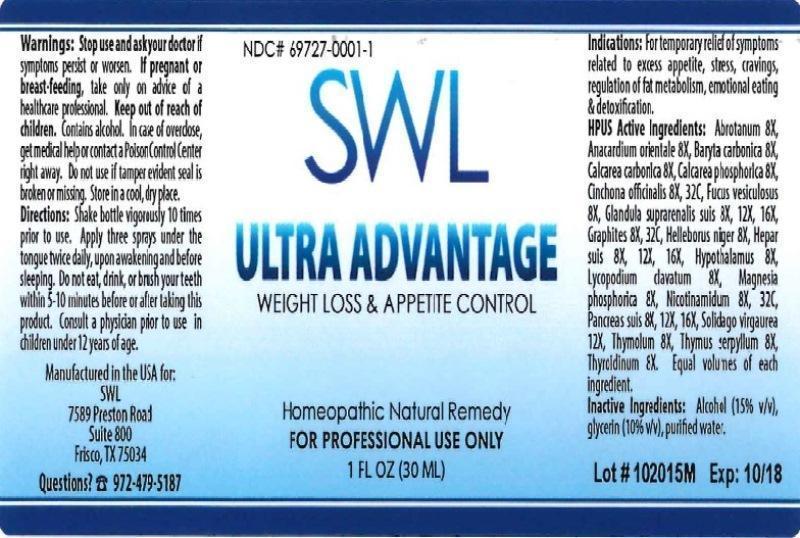 DRUG LABEL: SWL ULTRA ADVANTAGE
NDC: 69727-0001 | Form: LIQUID
Manufacturer: ELTTAC Inc DBA SWL
Category: homeopathic | Type: HUMAN OTC DRUG LABEL
Date: 20160503

ACTIVE INGREDIENTS: ARTEMISIA ABROTANUM FLOWERING TOP 8 [hp_X]/30 mL; SEMECARPUS ANACARDIUM JUICE 8 [hp_X]/30 mL; BARIUM CARBONATE 8 [hp_X]/30 mL; OYSTER SHELL CALCIUM CARBONATE, CRUDE 8 [hp_X]/30 mL; TRIBASIC CALCIUM PHOSPHATE 8 [hp_X]/30 mL; CINCHONA OFFICINALIS BARK 8 [hp_X]/30 mL; FUCUS VESICULOSUS 8 [hp_X]/30 mL; SUS SCROFA ADRENAL GLAND 8 [hp_X]/30 mL; GRAPHITE 8 [hp_X]/30 mL; HELLEBORUS NIGER ROOT 8 [hp_X]/30 mL; PORK LIVER 8 [hp_X]/30 mL; BOS TAURUS HYPOTHALAMUS 8 [hp_X]/30 mL; LYCOPODIUM CLAVATUM SPORE 8 [hp_X]/30 mL; MAGNESIUM PHOSPHATE, DIBASIC TRIHYDRATE 8 [hp_X]/30 mL; NIACINAMIDE 8 [hp_X]/30 mL; SUS SCROFA PANCREAS 8 [hp_X]/30 mL; SOLIDAGO VIRGAUREA FLOWERING TOP 12 [hp_X]/30 mL; THYMOL 8 [hp_X]/30 mL; THYMUS SERPYLLUM 8 [hp_X]/30 mL; THYROID, UNSPECIFIED 8 [hp_X]/30 mL
INACTIVE INGREDIENTS: ALCOHOL; GLYCERIN; WATER

SWL ULTRA ADVANTAGE

ACTIVE INGREDIENT

Active Ingredients: Abrotanum 8X, Anacardium orientale 8X, Baryta carbonica 8X, Calcarea carbonica 8X, Calcarea phosphorica 8X, Cinchona officinalis 8X, 32C, Fucus vesiculosus 8X, Glandula suprarenalis suis 8X, 12X, 16X, Graphites 8X, 32C, Helleborus niger 8X, Hepar suis 8X, 12X, 16X, Hypothalamus 8X, Lycopodium clavatum 8X, Magnesia phosphorica 8X, Nicotinamidum 8X, 32C, Pancreas suis 8X, 12X, 16X Solidago virgaurea 12X, Thymolum 8X, Thymus serpyllum 8X, Thyroidinum 8X.

INACTIVE INGREDIENT

Inactive ingredients: Alcohol (15 % v/v), glycerin (10 % v/v), purified water

INDICATIONS AND USAGE

Indications: For temporary relief of symptoms related to excess appetite, stress, cravings, regulation of fat metabolism, emotional eating & detoxification.

WARNINGS

Warnings: Stop use and ask your doctor if symptoms persist or worsen. If pregnant or breast-feeding, take only on advice of a healthcare professional. Keep out of reach of children. Contains alcohol. In case of overdose, get medical help or contact a Poison Control Center right away. Do not use if tamper evident seal is broken or missing. Store in a cool, dry place.

Keep out of reach of children.

DOSAGE AND ADMINISTRATION

Directions: Shake bottle vigorously 10 times prior to use. Apply three sprays under the tongue twice daily, upon awakening and before sleeping. Do not eat, drink, or brush your teeth within 5-10 minutes before or after taking this product. Consult a physician prior to use in children under 12 years of age.

PURPOSE

Indications: For temporary relief of symptoms related to:

- excess appetite
- stress, cravings
- regulation of fat metabolism
- emotional eating
- detoxification